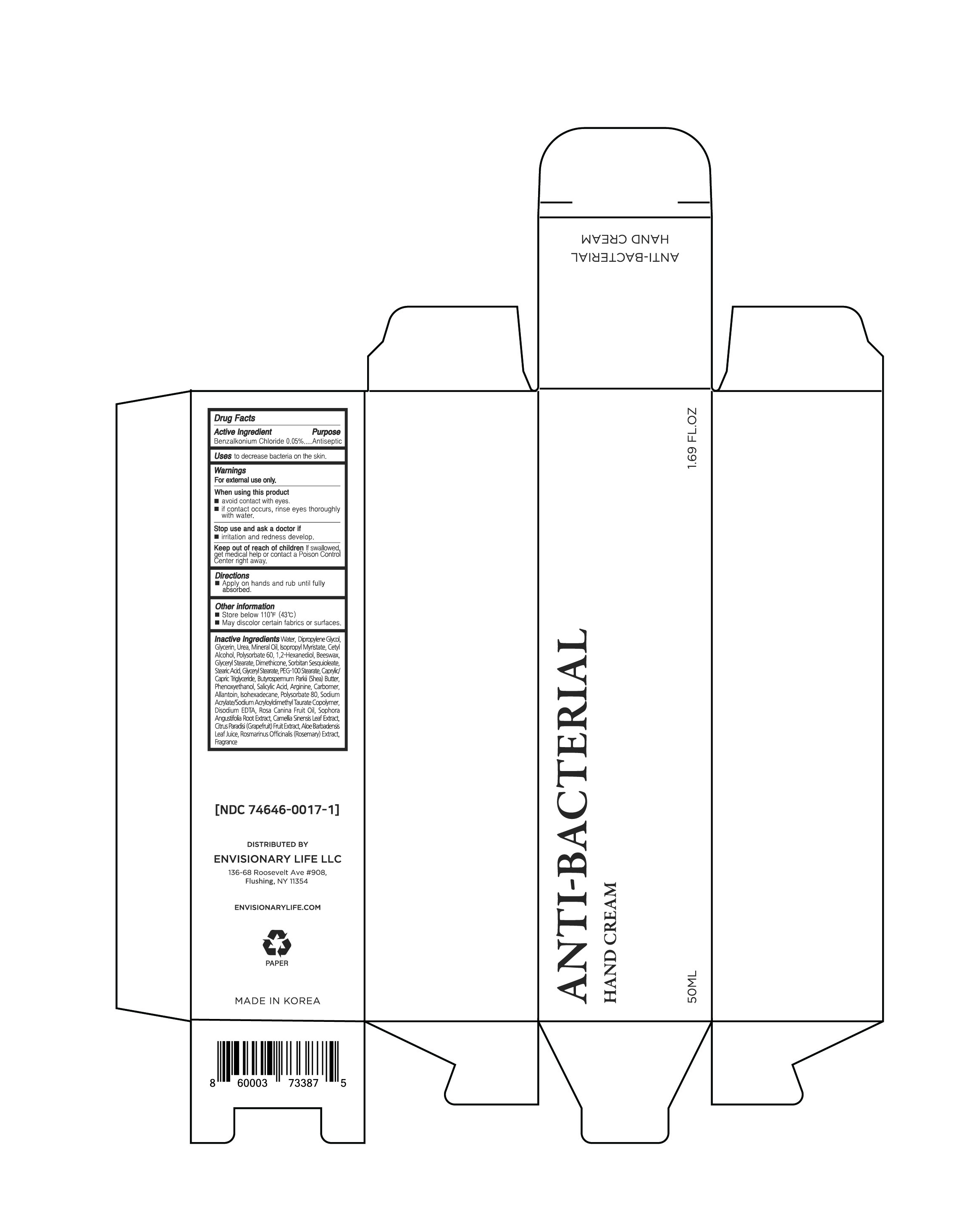 DRUG LABEL: ANTI-BACTERIAL HAND Cream
NDC: 74646-0017 | Form: CREAM
Manufacturer: Natural Korea Co., Ltd.
Category: otc | Type: HUMAN OTC DRUG LABEL
Date: 20210106

ACTIVE INGREDIENTS: BENZALKONIUM CHLORIDE 0.025 g/50 mL
INACTIVE INGREDIENTS: DIPROPYLENE GLYCOL; UREA; MINERAL OIL; ISOPROPYL MYRISTATE; 1,2-HEXANEDIOL; YELLOW WAX; GLYCERYL MONOSTEARATE; DIMETHICONE; SORBITAN SESQUIOLEATE; PEG-100 STEARATE; MEDIUM-CHAIN TRIGLYCERIDES; BUTYROSPERMUM PARKII (SHEA) BUTTER UNSAPONIFIABLES; PHENOXYETHANOL; SALICYLIC ACID; ARGININE; CARBOMER HOMOPOLYMER, UNSPECIFIED TYPE; ALLANTOIN; POLYSORBATE 80; EDETATE DISODIUM; ROSA CANINA FRUIT OIL; GREEN TEA LEAF; GRAPEFRUIT; ALOE VERA LEAF; CETYL ALCOHOL; STEARIC ACID; WATER; GLYCERIN; POLYSORBATE 60; ISOHEXADECANE; SOPHORA FLAVESCENS ROOT; ROSEMARY

ANTI-BACTERIAL HAND CREAM
50 mL
74646-0017-1